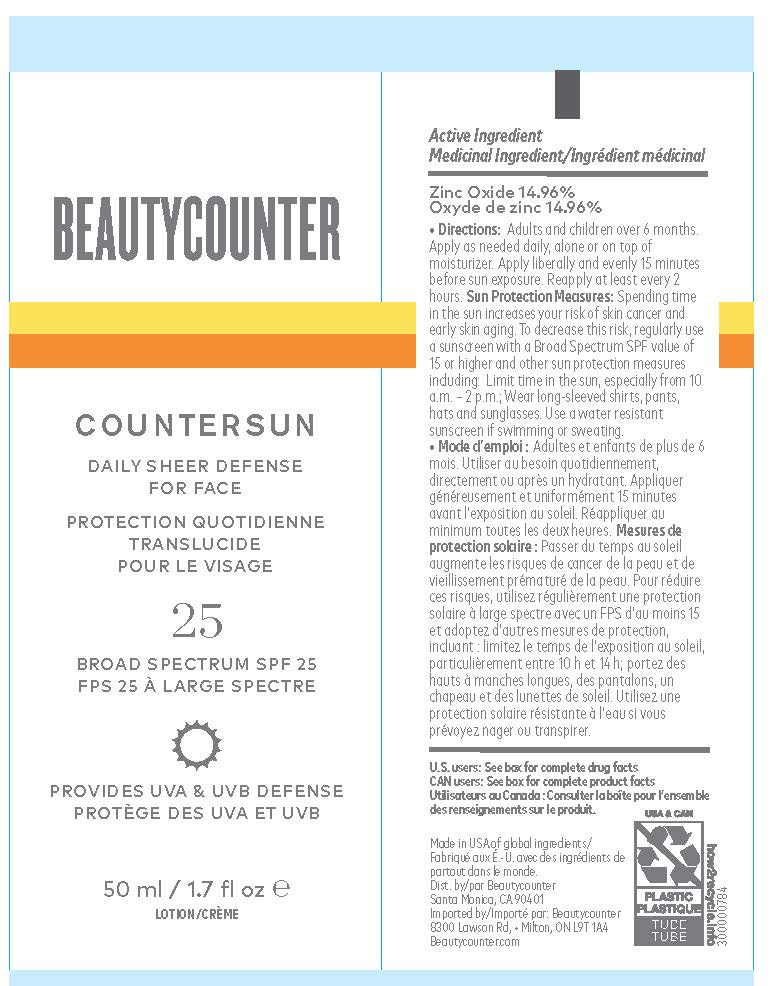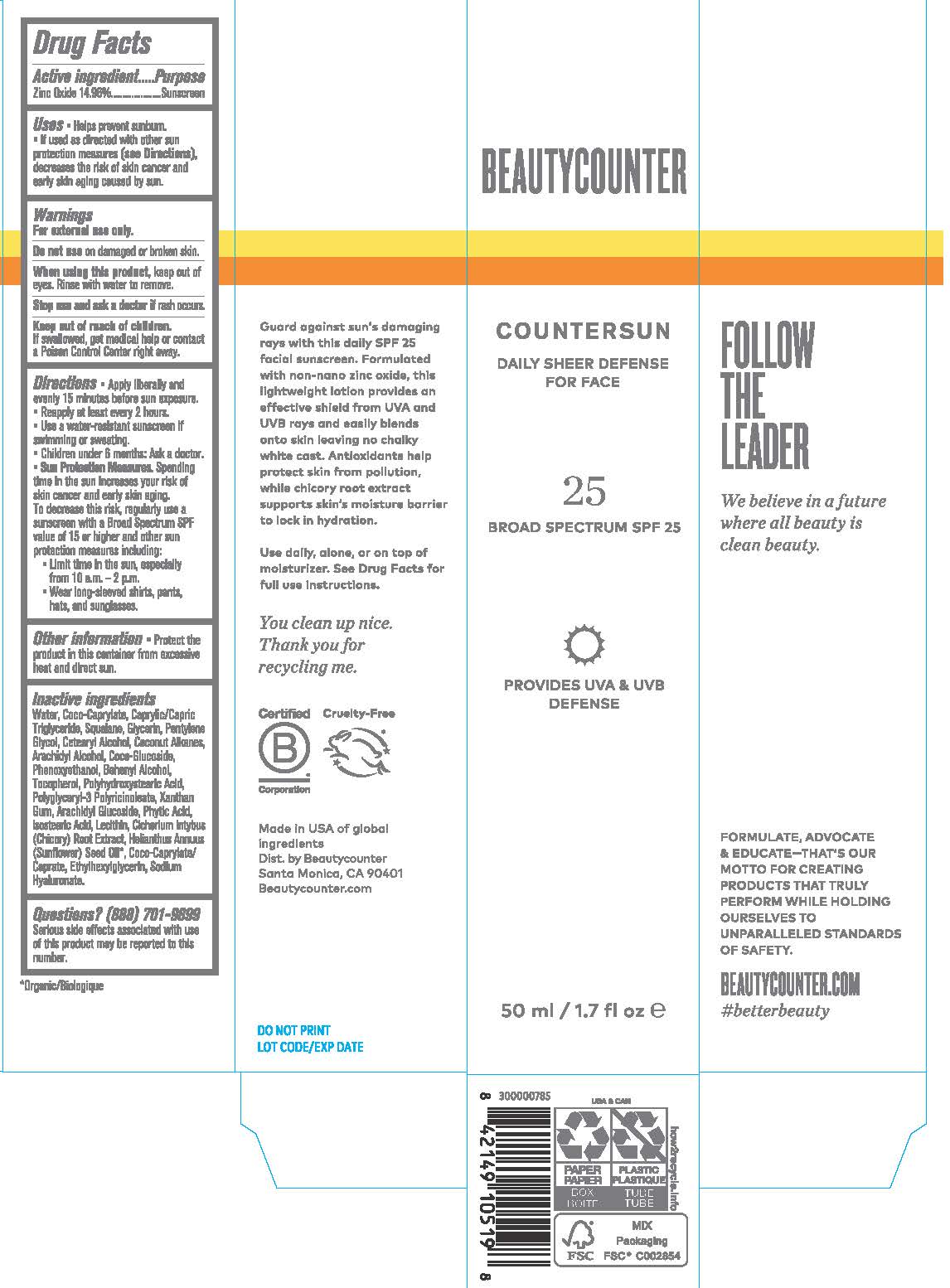 DRUG LABEL: BEAUTYCOUNTER COUNTERSUN  DAILY SHEER DEFENSE FOR FACE
NDC: 21839-615 | Form: LOTION
Manufacturer: Gordon Laboratories, Inc.
Category: otc | Type: HUMAN OTC DRUG LABEL
Date: 20200615

ACTIVE INGREDIENTS: ZINC OXIDE 149.6 mg/1 mL
INACTIVE INGREDIENTS: TOCOPHEROL; ARACHIDYL ALCOHOL; SQUALANE; COCO-CAPRYLATE; COCO-CAPRYLATE/CAPRATE; COCO GLUCOSIDE; COCONUT ALKANES; ETHYLHEXYLGLYCERIN; LECITHIN, SUNFLOWER; FYTIC ACID; HYALURONATE SODIUM; WATER; XANTHAN GUM; MEDIUM-CHAIN TRIGLYCERIDES; CHICORY ROOT; CETOSTEARYL ALCOHOL; GLYCERIN; SUNFLOWER OIL; ISOSTEARIC ACID; POLYGLYCERYL-3 RICINOLEATE; POLYHYDROXYSTEARIC ACID (2300 MW); PENTYLENE GLYCOL; PHENOXYETHANOL; ARACHIDYL GLUCOSIDE; DOCOSANOL

BEAUTYCOUNTER COUNTERSUN DAILY SHEER DEFENSE FOR FACE

DRUG FACTS

Active ingredient

Zinc Oxide 14.96%

Purpose

Sunscreen

INDICATIONS AND USAGE

Uses * Helps prevent sunburn.

* If used as directed with other sun protection (see Directions), decreases the risk of skin cancer and early skin aging caused by sun.

WARNINGS

For external use only.

-------------------------------------------------------

Do not use on damaged or broken skin.

-------------------------------------------------------
When using this product, keep out of

eyes. Rinse with water to remove.

-------------------------------------------------------
Stop use and ask a doctor if rash occurs.

------------------------------------------------------

Keep out of reach of children.

If swallowed, get medical help or contact

a Poison Control Center right away.

Do not use on damaged or broken skin.

When using this product, keep out of eyes. Rinse with water to remove.

Stop use and ask a doctor if rash occurs.

Keep out of reach of children.

If swallowed, get medical help or contact a Poison Control Center right away.

DIRECTIONS

Directions *Apply liberally and

evenly 15 minutes before sun exposure.

* Reapply at least every 2 hours.

* Use a water-resistant sunscreen if

swimming or sweating.

* Children under 6 months: Ask a doctor.

* Sun Protection Measures. Spending

time in the sun increases your risk of

skin cancer and early skin aging.

To decrease this risk, regularly usa a

sunscreen with a Broad Spectrum SPF

value of 15 or higher and other sun

protection measures including:

* Limit time in the sun, especially

from 10 a.m. - 2 p.m.

* Wear long-sleeved shirts, pants,

hats and sunglasses.

OTHER INFORMATION

Other information * Protect the

product in this container from excessive

heat and direct sun.

INACTIVE INGREDIENTS

Water, Coco-Caprylate, Caprylic/Capric Triglyceride, Squalane, Glycerin, Pentylene Glycol, Cetearyl Alcohol, Coconut Alkanes, Arachidyl Alcohol, Coco-Glucoside, Phenoxyethanol, Behenyl Alcohol, Tocopherol, Polyhydroxystearic Acid, Polyglyceryl-3 Polyricinoleate, Xanthan Gum, Arachidyl Glucoside, Phytic Acid, Isostearic Acid, Lecithin, Cichorium Intybus (Chicory) Root Extract, Helianthus Annuus (Sunflower) Seed Oil*, Coco-Caprylate/Caprate, Ethylhexylglycerin, Sodium Hyaluronate.

*Organic

QUESTIONS

Questions? (888) 701-9899

Serious side effects associated with use

of this product may be reported to this number.